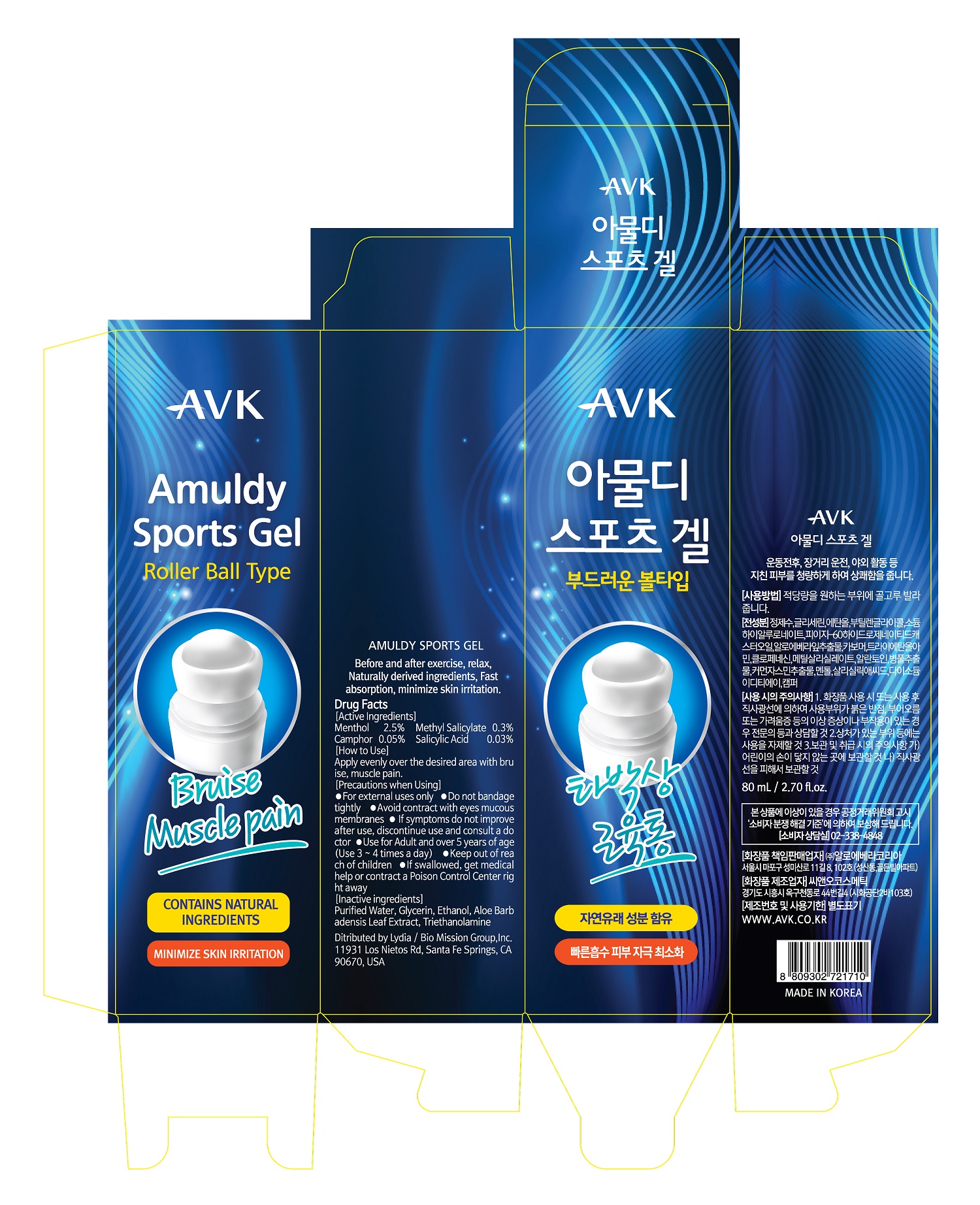 DRUG LABEL: AMULDY SPORTS gel
NDC: 72988-0023 | Form: LIQUID
Manufacturer: Lydia Co., Ltd.
Category: otc | Type: HUMAN OTC DRUG LABEL
Date: 20230706

ACTIVE INGREDIENTS: METHYL SALICYLATE 0.3 g/100 mL; MENTHOL 2.5 g/100 mL; SALICYLIC ACID 0.03 g/100 mL; CAMPHOR OIL 0.05 g/100 mL
INACTIVE INGREDIENTS: WATER

Drug Facts

ACTIVE INGREDIENT

menthol

INACTIVE INGREDIENT

water, glycerin, etc

PURPOSE

before and after exercise, relax, naturally derived ingredients, fast absorption, minimize skin irritation

keep out of reach of the children

INDICATIONS AND USAGE

apply evenly over the desired area with bruise, muscle pain

WARNINGS

don’t use on the part where there is injury, eczema, or dermatitis

if swallowed, get medical help or contact a person control center immediately

DOSAGE AND ADMINISTRATION

for topical use only